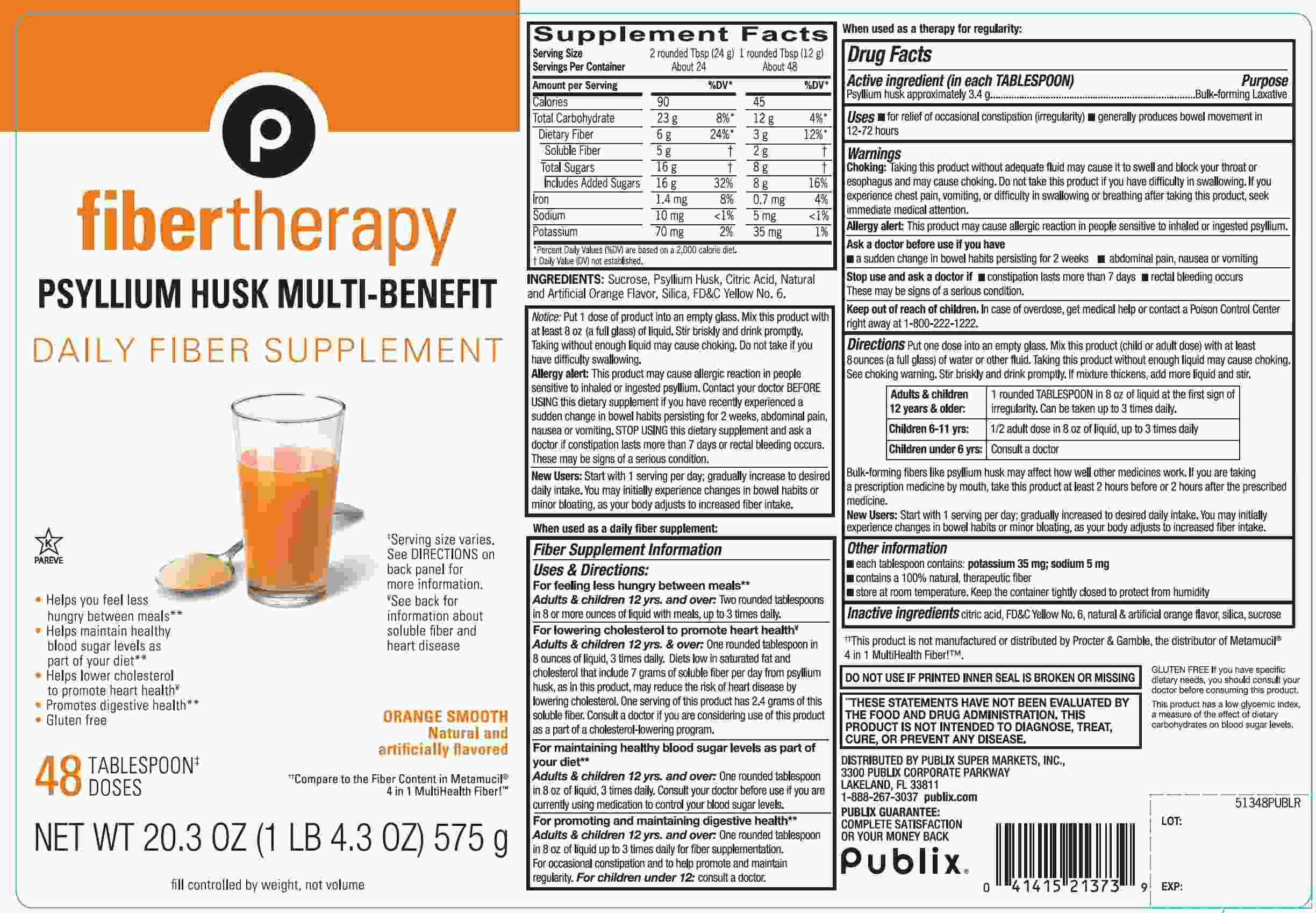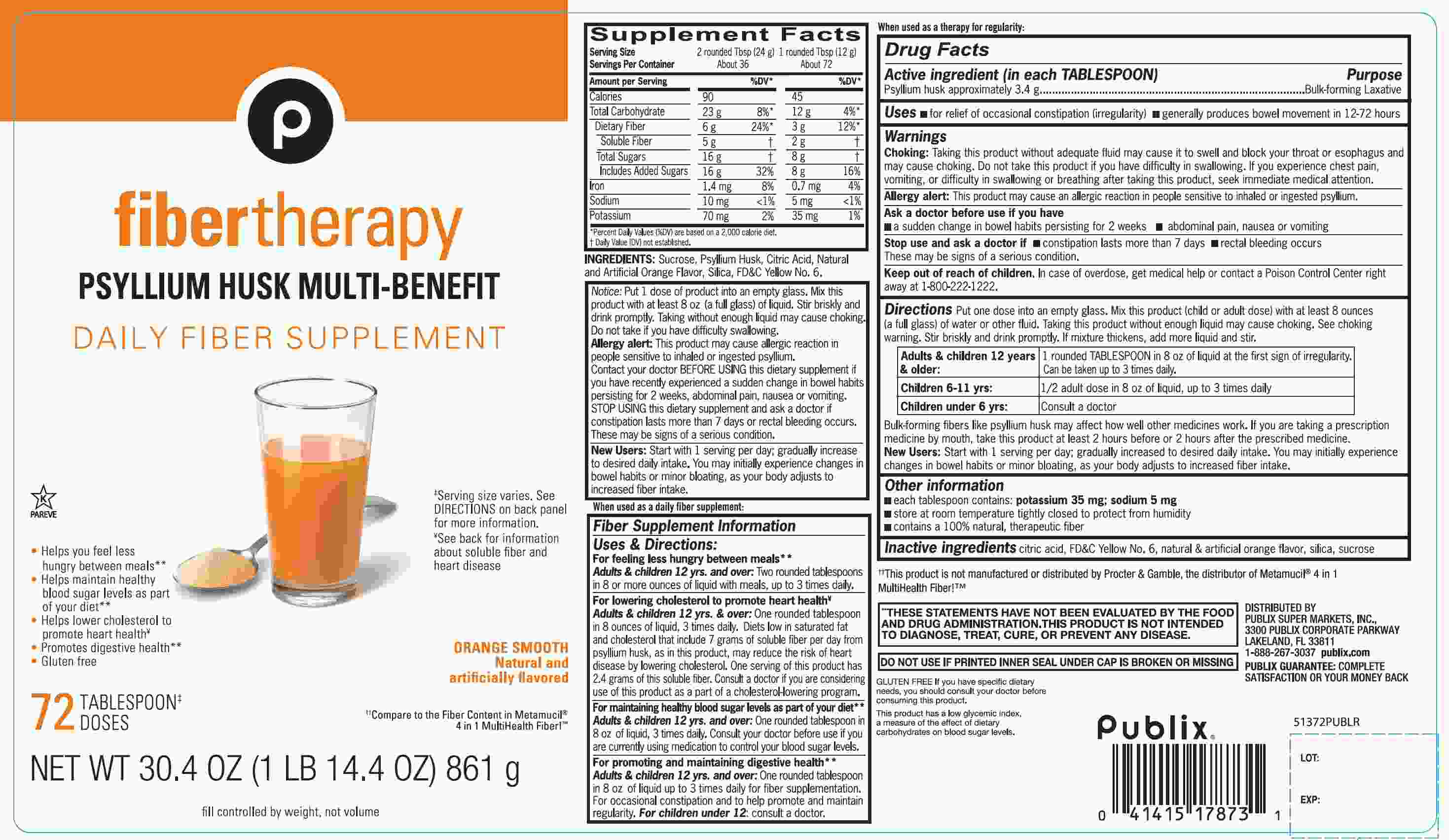 DRUG LABEL: Publix Fiber Therapy

NDC: 41415-513 | Form: POWDER
Manufacturer: PUBLIX SUPER MARKETS, INC
Category: otc | Type: HUMAN OTC DRUG LABEL
Date: 20251028

ACTIVE INGREDIENTS: PSYLLIUM HUSK 3.4 g/12 g
INACTIVE INGREDIENTS: ANHYDROUS CITRIC ACID; FD&C YELLOW NO. 6; SILICON DIOXIDE; SUCROSE

Publix Fiber Therapy Psyllium Husk Orange Smooth

Drug Facts

Active ingredient: (in each TABLESPOON)

Psyllium husk approximately 3.4 g

Purpose

Bulk-forming Laxative

Uses:

- for relief of occasional constipation (irregularity)
- generally produces bowel movement in 12-72 hours

Warnings:

Choking

Taking this product without adequate fluid may cause it to swell and block your throat or esophagus and may cause choking. Do not take this product if you have difficulty in swallowing. If you experience chest pain, vomiting, or difficulty in swallowing or breathing after taking this product, seek immediate medical attention.

Allergy alert:

This product may cause allergic reaction in people sensitive to inhaled or ingested psyllium.

Ask a doctor before use if you have

- a sudden change in bowel habits persisting for 2 weeks
- abdominal pain, nausea or vomiting

Stop use and ask a doctor if

- constipation lasts more than 7 days
- rectal bleeding occurs

These may be signs of a serious condition.

Keep out of reach of children.In case of overdose, get medical help or contact a Poison Control Center right away at 1-800-222-1222.

Directions:

Put one dose into an empty glass. Mix this product (child or adult dose) with at least 8 ounces (a full glass) of water or other fluid. Taking this product without enough liquid may cause choking. See choking warning. Stir briskly and drink promptly. If mixture thickens, add more liquid and stir.

Adults & children 12 years & older: | 1 rounded TABLESPOON in 8 oz of liquid at the first sign of irregularity. Can be taken up to 3 times daily.
Children 6 – 11 yrs : | ½ adult dose in 8 oz of liquid, up to 3 times daily
Children Under 6 yrs: | Consult a doctor

Bulk forming fibers like psyllium husk may affect how well other medicines work. If you are taking a prescription medicine by mouth, take this product at least 2 hours before or 2 hours after the prescribed medicine.

New Users

Start with 1 serving per day; gradually increased to desired daily intake. You may initially experience changes in bowel habits or minor bloating, as your body adjusts to increased fiber intake.

Other information:

- each tablespoon contains: potassium 35 mg; sodium 5 mg
- store at room temperature. tightly closed to protect from humidity
- contains a 100% natural, therapeutic fiber

Inactive ingredients

citric acid, FD &C yellow 6, natural and artificial orange flavor, silica, sucrose

Questions or comments?

1-866-467-2748

PRINCIPAL DISPLAY PANEL

††Compare to the Fiber Content in Metamucil®4 in 1 MultiHealth Fiber!™

Fiber therapy

PSYLLIUM HUSK MULTI- BENEFIT

DAILY FIBER SUPPLEMENT

ORANGE SMOOTH

Natural and artificially flavored

- Helps you feel less hungrybetween meals**
- Helps maintain healthy blood sugarlevels as part of your diet **
- Helps lower cholesterolto promote heart health**
- Promotes digestive health**
- Gluten free

fill controlled by weight, not volume

†See back for information about soluble fiber and heart disease.

‡Serving size varies. See DIRECTIONS on back panel for more information

**THESE STATEMENTS HAVE NOT BEEN EVALUATED BY THE FOOD AND DRUG ADMINISTRATION. THIS PRODUCT IS NOT INTENDED TO DIAGNOSE, TREAT, CURE OR PREVENT ANY DISEASE.

DO NOT USE IF PRINTED INNER SEAL IS BROKEN OR MISSING

*This product is not manufactured or distributed by Procter & Gamble Company, Owner of the registered trademark Metamucil ®.

GLUTEN FREE If you have specific dietary needs, you should consult your doctor before consuming this product.

This product has a low glycemic index, a measure of the effect of dietary carbohydrates on blood sugar levels.

DISTRIBUTED BY

PUBLIX SUPER MARKETS, INC.,

3300 PUBLIX CORPORATE PARKWAY

LAKELAND. FL 33811

1-888-267-3037 publix.com

PUBLIX GUARANTEE:CPMPLETE SATISFACTION OR YOUR MONEY BACK

PACKAGE LABEL 72 TABLESPOON DOSES